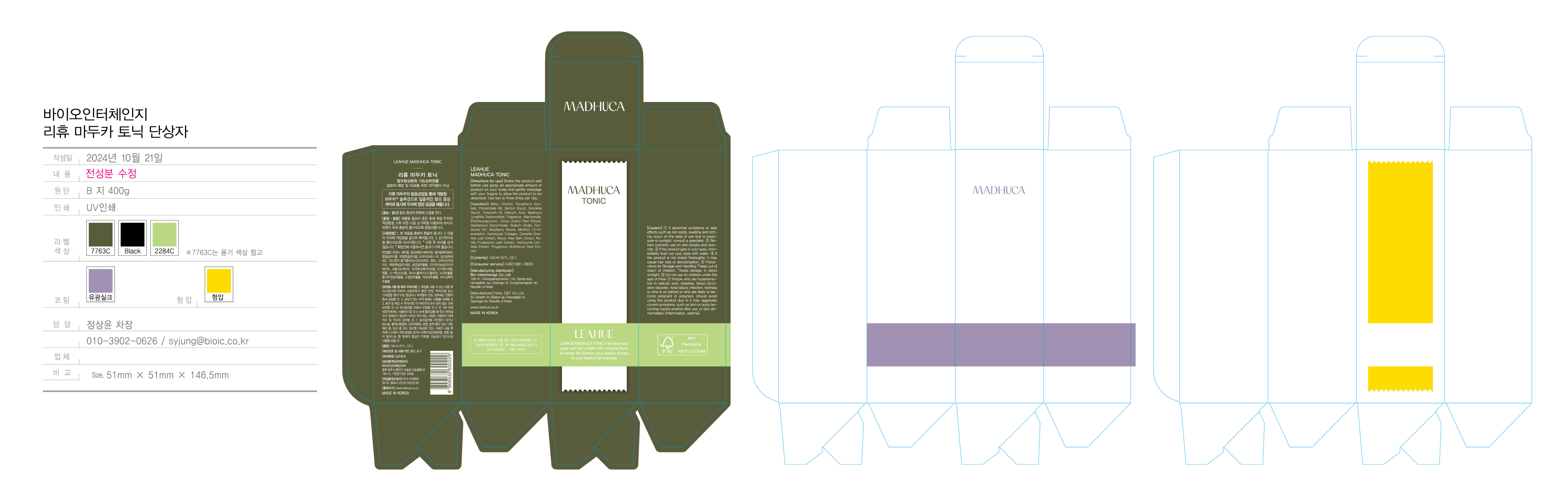 DRUG LABEL: LEAHUE MADHUCA TONIC
NDC: 72837-0003 | Form: LIQUID
Manufacturer: Bio-interchange Co.
Category: otc | Type: HUMAN OTC DRUG LABEL
Date: 20250404

ACTIVE INGREDIENTS: SALICYLIC ACID 0.6 g/100 mL
INACTIVE INGREDIENTS: MENTHOL; ALCOHOL

Active Ingredient

Salicylic Acid

Inactive Ingredients

Menthol, Water, Alcohol, etc

Purpose

Leahue Tonic helps to relieve the symptoms of hair loss, dandruff, and utching while provides a moist and shiny hair.

Keep out of reach of children

Indications & Usage

Shake the product well before use. Spray an appropriate amount of product on your scalp and gently massage with your fingers to allow the product to be absorbed. Use two to three times per day.

Warnings (Cautions)

1. Stop use and ask a doctor incase. *condition worsens. *redness is present. *irritation develops.
2. Don’t apply to wounded or damaged skin.
3. When using this product. *use only as directed. *avoid contact with eyes.
4. Handle & Precautions 1) Keep out of reach of children. 2) For external use only. Store at room temperature.
5. If you have a history of allergic symptoms, consult your doctor and/or pharmacist before use.
6. Do not use this product on children under the age of three.
7. Persons who have hypersensitivity to salicylate, diabetes, poor blood circulation, kidney failure, infection, inflammation, skin abnormalities, and/or pregnant or likely to become pregnant should not use this product.

DOSAGE AND ADMINISTRATION

For external use only